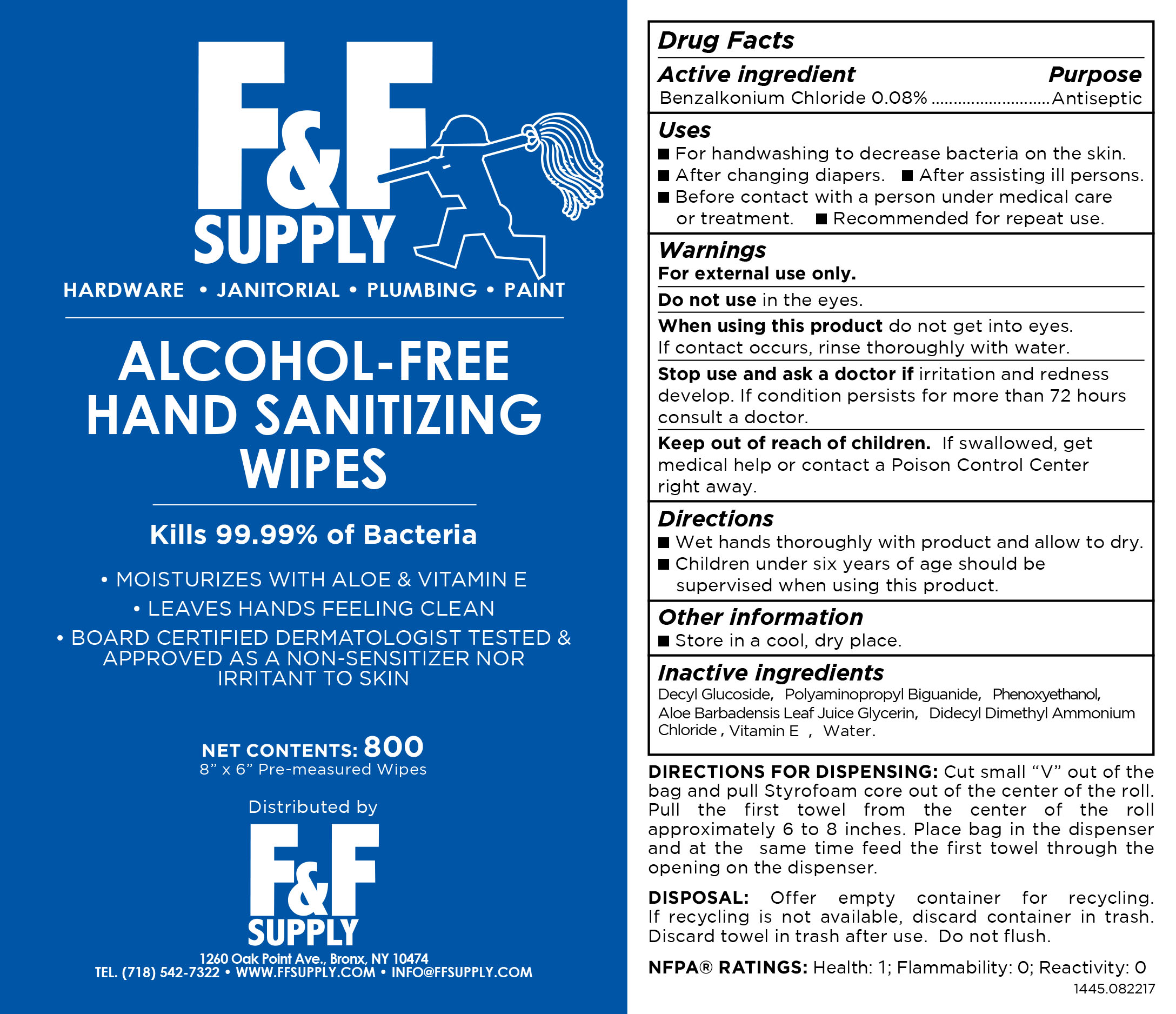 DRUG LABEL: Alcohol Free Hand Sanitizing Wipes
NDC: 71766-006 | Form: SWAB
Manufacturer: Hangzhou Linkeweier Daily Chemicals Co. Ltd.
Category: otc | Type: HUMAN OTC DRUG LABEL
Date: 20210303

ACTIVE INGREDIENTS: BENZALKONIUM CHLORIDE 0.08 1/100 1
INACTIVE INGREDIENTS: DECYL GLUCOSIDE; PHENOXYETHANOL; POLYAMINOPROPYL BIGUANIDE; .ALPHA.-TOCOPHEROL ACETATE; DIDECYLDIMONIUM CHLORIDE; WATER; ALOE VERA LEAF

Alcohol Free Hand Sanitizing Wipes

ACTIVE INGREDIENT

Benzalkonium chloride 0.08%

PURPOSE

Antiseptic

USES

- For handwashing to decrease bacteria on the skin.
- After changing diapers.
- After assisting ill persons.
- Before contact with a person under medical care or treatment.
- Recommended for repeat use.

WARNING

For external use only.

Do not use in the eyes.

When using this product do not get into eyes. If contact occurs, rinse thoroughly with water.

Stop use and ask a doctor if irritation and redness develop. If condition persists for more than 72 hours consult a doctor.

KEEP OUT OF REACH OF CHILDREN

Keep out of reach from children. If swallowed, get medical help or contact a Poison Control Center right away.

DIRECTIONS

- Wet hands thoroughly with product and allow to dry.
- Children under six years of age should be supervised when using this product.

OTHER INFORMATION

Store in a cool, dry place.

INACTIVE INGREDIENT

Decyl Glucoside，Polyaminopropyl Biguanide，Phenoxyethanol， Didecyl Dimethyl Ammonium Chloride，Aloe Barbadensis Leaf Juice Glyceri，Vitamin E, Water

PACKAGE LABEL

800 IN A BAG NDC: 71766-006-01